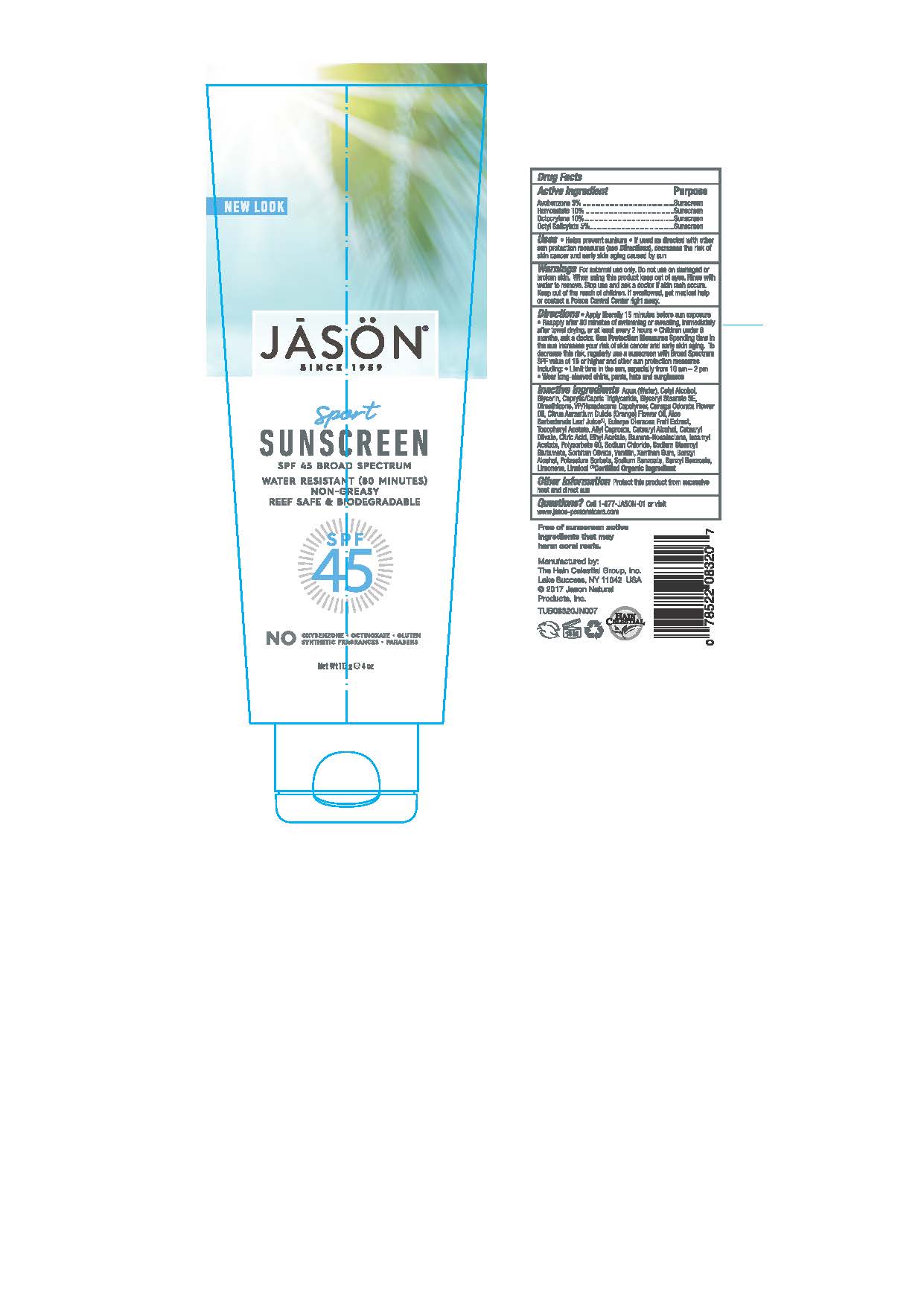 DRUG LABEL: J0832014 Jason Sun Sport Sunscreen SPF45
NDC: 61995-0020 | Form: LOTION
Manufacturer: The Hain Celestial Group, Inc.
Category: otc | Type: HUMAN OTC DRUG LABEL
Date: 20210205

ACTIVE INGREDIENTS: HOMOSALATE 10 g/100 g; OCTISALATE 5 g/100 g; OCTOCRYLENE 10 g/100 g; AVOBENZONE 3 g/100 g
INACTIVE INGREDIENTS: ACAI; CITRIC ACID MONOHYDRATE; ETHYLHEXYLGLYCERIN; BENZYL ALCOHOL; PHENOXYETHANOL; ALOE VERA LEAF; GLYCERIN; WATER; SODIUM STEAROYL GLUTAMATE; .ALPHA.-TOCOPHEROL ACETATE; GLYCERYL STEARATE SE; POTASSIUM SORBATE; CETYL ALCOHOL; DIMETHICONE; XANTHAN GUM; CETOSTEARYL ALCOHOL; VINYLPYRROLIDONE/HEXADECENE COPOLYMER; POLYSORBATE 60; MEDIUM-CHAIN TRIGLYCERIDES; CETEARYL OLIVATE; ORANGE OIL; SODIUM CHLORIDE; SORBITAN OLIVATE; SODIUM BENZOATE; CANANGA OIL

J0832014 Jason Sun Sport Sunscreen SPF45

ACTIVE INGREDIENT

Avobenzone -3.0%

Homosalate - 10.0%

Octocrylene - 10.0%

Octyl Salicylate - 5.0%

DOSAGE AND ADMINISTRATION

Apply liberally 15 minutes before sun exposure. Reapply after 80 minutes of swimming or sweating, immediately after towel drying and at least every 2 hours. Children under 6 months, ask a doctor.

PURPOSE

Sunscreen

WARNINGS

For external use only. Do not use on damaged or broken skin. When using this product keep out of eyes. Rinse with water to remove. Stop use and ask a doctor if skin rash occurs.

Keep out of reach of children. If swallowed get medical help or contact Poison Center right away.

INACTIVE INGREDIENT

Water, Cetyl Alcohol, Glycerin, Caprylic/Capric Triglyceride,Glyceryl Stearate SE Dimethicone,VP/Hexadecene Copolymer, Cetearyl Alcohol, Aloe Barbadensis Leaf Juice(1), Cananga Odorate Flower Oil, Citrus Aurantium Dulcis (Orange0 Flower Oil, Euterpe Olearacea Fruit Extract, Cetearyl Olivate, Polysorbate 60, Sodium Chloride, Sodium Stearoyl Glutamate, Sorbitan Olivate, Tocopheryl Acetate, Xanthan Gum, Citric Acid, Benzyl Alcohol, Ethylhexylglycerin, Phenoxyethanol, Potassium Sorbate, Sodium Benzoate.

(1) Certified Organic Ingredient

INDICATIONS AND USAGE

Helps prevents sunburns. If used as directed with other sun protection measures, decreases risk of skin cancer and early skin aging caused by sun exposure. Skin Protection Measures: Spending time in the sun increases your risk of skin cancer and early skin aging. To decrease risk, regularly use sunscreen with Broad Spectrum SPF 15 or higher and other protective measures including: limit time in sun, especially from10am to 2pm, and wear long sleeved shirts, pants, hats and sunglases.